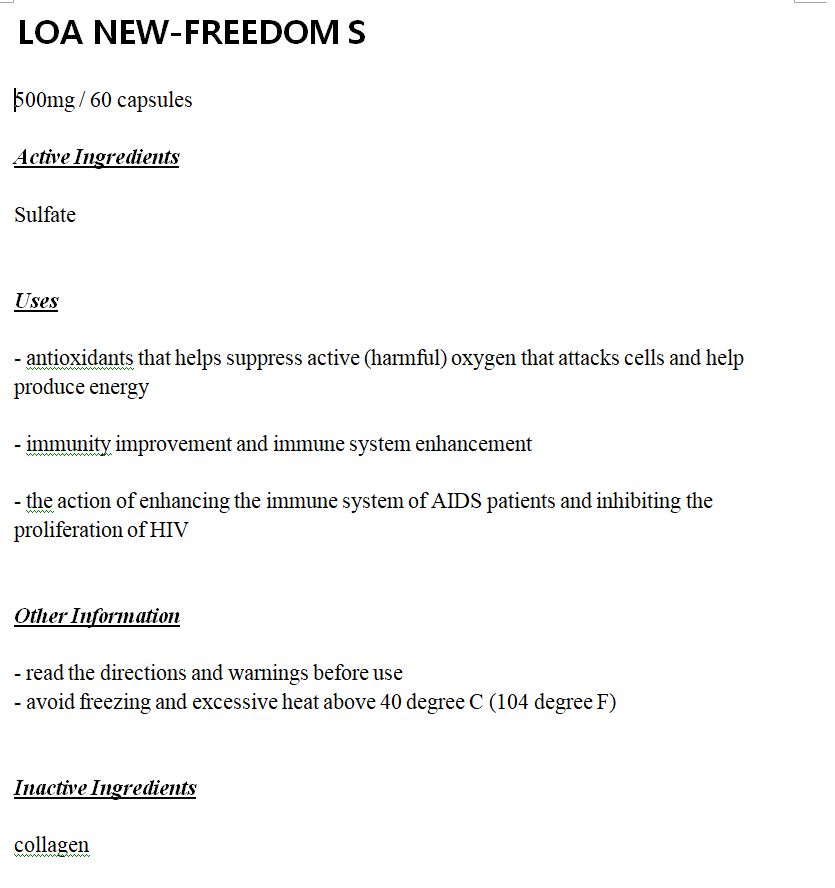 DRUG LABEL: LOA NEW-FREEDOM S
NDC: 81841-0001 | Form: CAPSULE
Manufacturer: CO LTD JUNG MIN
Category: otc | Type: HUMAN OTC DRUG LABEL
Date: 20210424

ACTIVE INGREDIENTS: SULFATE ION 100 g/100 1
INACTIVE INGREDIENTS: WATER

Drug Facts

ACTIVE INGREDIENT

sulfate

INACTIVE INGREDIENT

sulfate

PURPOSE

anti oxident, anti inflammatory

KEEP OUT OF REACH OF THE CHILDREN

INDICATIONS AND USAGE

take one capsule two times per day with water

WARNINGS

store in a cool dry place

DOSAGE AND ADMINISTRATION

for oral use only